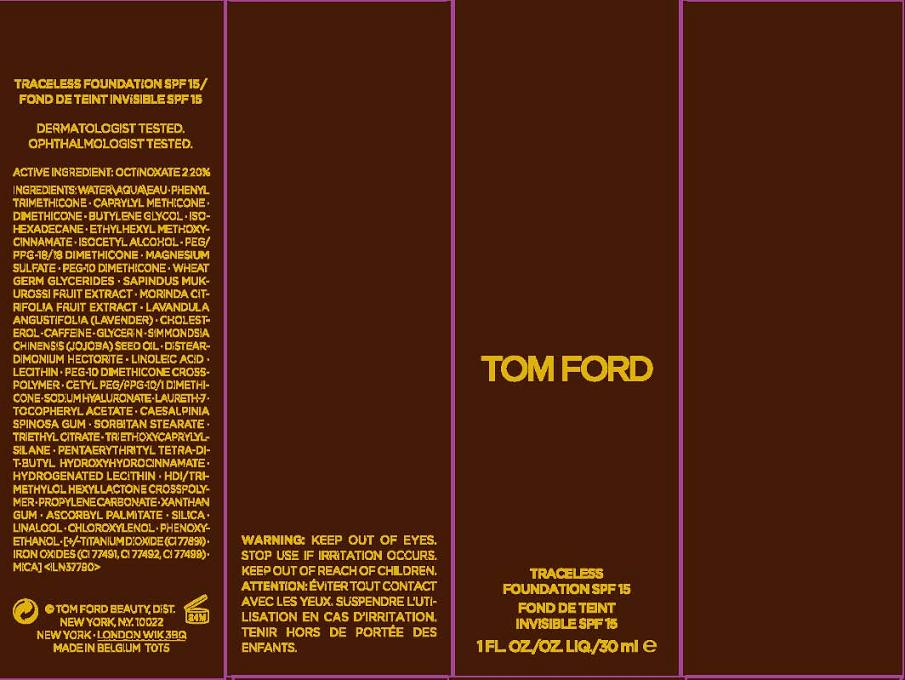 DRUG LABEL: TOM FORD TRACELESS FOUNDATION
NDC: 62872-766 | Form: LIQUID
Manufacturer: ESTEE LAUDER N.V.
Category: otc | Type: HUMAN OTC DRUG LABEL
Date: 20110825

ACTIVE INGREDIENTS: OCTINOXATE 2.2 mL/100 mL
INACTIVE INGREDIENTS: WATER; PHENYL TRIMETHICONE; DIMETHICONE; BUTYLENE GLYCOL; ISOHEXADECANE; MEDIUM-CHAIN TRIGLYCERIDES; ISOCETYL ALCOHOL; MAGNESIUM SULFATE, UNSPECIFIED; WHEAT GERM OIL; SAPINDUS MUKOROSSI FRUIT; MORINDA CITRIFOLIA FRUIT; LAVANDULA ANGUSTIFOLIA FLOWER; CHOLESTEROL; CAFFEINE; GLYCERIN; JOJOBA OIL; LINOLEIC ACID; LECITHIN, SOYBEAN; HYALURONATE SODIUM; LAURETH-7; ALPHA-TOCOPHEROL ACETATE; CAESALPINIA SPINOSA RESIN; SORBITAN MONOSTEARATE; TRIETHYL CITRATE; TRIETHOXYCAPRYLYLSILANE; HYDROGENATED SOYBEAN LECITHIN; PROPYLENE CARBONATE; XANTHAN GUM; ASCORBYL PALMITATE; SILICON DIOXIDE; CHLOROXYLENOL; PHENOXYETHANOL; TITANIUM DIOXIDE; MICA; FERRIC OXIDE RED

ACTIVE INGREDIENT: OCTINOXATE 2.20%

INACTIVE INGREDIENT

INACTIVE INGREDIENTS: WATER\AQUA\EAU [] PHENYL TRIMETHICONE [] CAPRYLYL METHICONE [] DIMETHICONE [] BUTYLENE GLYCOL [] ISOHEXADECANE [] CAPRYLIC/CAPRIC TRIGLYCERIDE [] ISOCETYL ALCOHOL [] PEG/PPG-18/18 DIMETHICONE [] MAGNESIUM SULFATE [] PEG-10 DIMETHICONE [] WHEAT GERM GLYCERIDES [] SAPINDUS MUKUROSSI FRUIT EXTRACT [] MORINDA CITRIFOLIA FRUIT EXTRACT [] LAVANDULA ANGUSTIFOLIA (LAVENDER) [] CHOLESTEROL [] CAFFEINE [] GLYCERIN [] SIMMONDSIA CHINENSIS (JOJOBA) SEED OIL [] DISTEARDIMONIUM HECTORITE [] LINOLEIC ACID [] LECITHIN [] PEG-10 DIMETHICONE CROSSPOLYMER [] CETYL PEG/PPG-10/1 DIMETHICONE [] SODIUM HYALURONATE [] LAURETH-7 [] TOCOPHERYL ACETATE [] CAESALPINIA SPINOSA GUM [] SORBITAN STEARATE [] TRIETHYL CITRATE [] TRIETHOXYCAPRYLYLSILANE [] PENTAERYTHRITYL TETRA-DI-T-BUTYL HYDROXYHYDROCINNAMATE [] HYDROGENATED LECITHIN [] HDI/TRIMETHYLOL HEXYLLACTONE CROSSPOLYMER [] PROPYLENE CARBONATE [] XANTHAN GUM [] ASCORBYL PALMITATE [] SILICA [] LINALOOL [] CHLOROXYLENOL [] PHENOXYETHANOL [] [+/- TITANIUM DIOXIDE (CI 77891) [] IRON OXIDES (CI 77491, CI 77492, CI 77499) [] MICA]

WARNINGS

WARNING: KEEP OUT OF EYES. DISCONTINUE USE IF IRRITATION OCCURS. KEEP OUT OF REACH OF CHILDREN.

PACKAGE LABEL

PRINCIPAL DISPLAY PANEL:

TOM FORD

TRACELESS FOUNDATION SPF 15

1 FL OZ LIQ/30 ML

TOM FORD BEAUTY DISTR.

NEW YORK, NY 10022

MADE IN BELGIUM